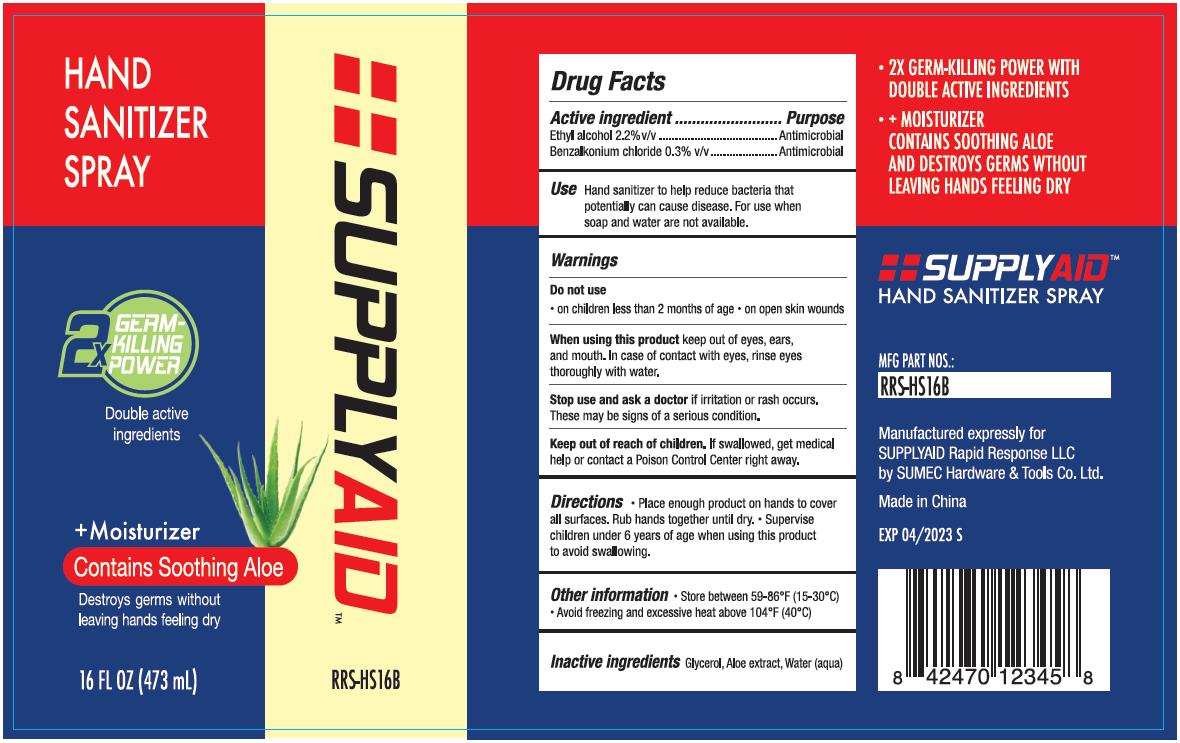 DRUG LABEL: SUPPLYAID Hand sanitizer RRS-HS16B
NDC: 74035-1017 | Form: LIQUID
Manufacturer: SUMEC Hardware & Tools Co., Ltd.
Category: otc | Type: HUMAN OTC DRUG LABEL
Date: 20200417

ACTIVE INGREDIENTS: BENZALKONIUM CHLORIDE 1.419 g/473 mL; ALCOHOL 10.406 mL/473 mL
INACTIVE INGREDIENTS: ALOE VERA LEAF 0.2365 mL/473 mL; WATER 458.5735 mL/473 mL; GLYCERIN 2.365 mL/473 mL

SUMEC, Hand Sanitizer, Liquid, 2.2% Ethyl alcohol, 473mL

Active Ingredient(s)

Alcohol 2.2% v/v. Purpose: Antiseptic

Purpose

Antiseptic, Hand Sanitizer

Use

Hand Sanitizer to help reduce bacteria that potentially can cause disease. For use when soap and water are not available.

Warnings

Flammable. For external use only. Keep away from heat or flame.

Do not use

- on children less than 2 months of age
- on open skin wounds

When using this product keep out of eyes, ears, and mouth.

In case of contact with eyes, rinse eyes thoroughly with water.

Stop use and ask a doctor if irritation or rash occurs. These may be signs of a serious condition.

Keep out of reach of children. If swallowed, get medical help or contact a Poison Control Center right away.

Directions

- Place enough product on hands to cover all surfaces. Rub hands together until dry.
- Supervise children under 6 years of age when using this product to avoid swallowing.

Other information

- Store between 59-86℉ (15-30℃)
- Avoid freezing and excessive heat above 104℉ (40℃)

Inactive ingredients

Glycerol, Aloe extract, Water (aqua)